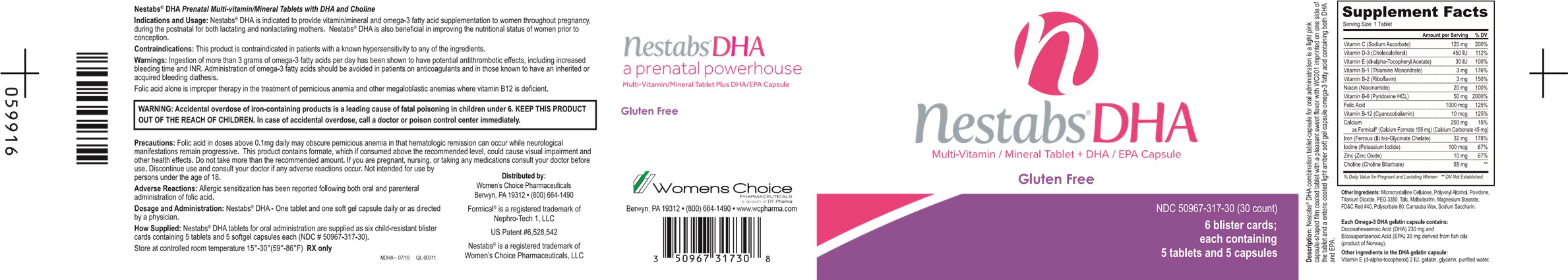 DRUG LABEL: NESTABS DHA
NDC: 50967-317 | Form: KIT | Route: ORAL
Manufacturer: WOMENS CHOICE PHARMACEUTICALS LLC
Category: prescription | Type: HUMAN PRESCRIPTION DRUG LABEL
Date: 20250428

ACTIVE INGREDIENTS: THIAMINE MONONITRATE 3 mg/1 1; RIBOFLAVIN 3 mg/1 1; NIACINAMIDE 20 mg/1 1; PYRIDOXINE HYDROCHLORIDE 50 mg/1 1; FOLIC ACID 1 mg/1 1; CYANOCOBALAMIN 10 ug/1 1; CALCIUM FORMATE 155 mg/1 1; CALCIUM CARBONATE 45 mg/1 1; FERROUS BISGLYCINATE 32 mg/1 1; SODIUM ASCORBATE 120 mg/1 1; CHOLECALCIFEROL 450 [iU]/1 1; ALPHA-TOCOPHERYLQUINONE 30 [iU]/1 1; POTASSIUM IODIDE 100 ug/1 1; ZINC OXIDE 10 mg/1 1; CHOLINE BITARTRATE 55 mg/1 1; DOCONEXENT 230 mg/1 1; ICOSAPENT 30 mg/1 1; .ALPHA.-TOCOPHEROL, D- 2 [iU]/1 1
INACTIVE INGREDIENTS: CELLULOSE, MICROCRYSTALLINE; MAGNESIUM STEARATE; POVIDONE; POLYVINYL ALCOHOL; TITANIUM DIOXIDE; TALC; FD&C RED NO. 40; ALUMINUM OXIDE; SACCHARIN; GELATIN; GLYCERIN; WATER

NESTABS DHA Prenatal Multi-vitamin/Mineral Tablet

DESCRIPTION

D escripton: Nestabs DHA combination tablet-capsule for oral administration is a light pink capsule-shaped film coated tablet with a pleasant sweet flavor with WCOO1 imprinted on one side of the tablet and a enteric coated light amber soft gel capsule omega-3 fatty acid containing both DHA and EPA.

INDICATIONS AND USAGE

I ndications and Usage: Nestabs DHA is indicated to provide vitamin/mineral and omega-3 fatty acid supplementation to women throughout pregnancy, during the postnatal for both lactating and nonlactating mothers. Nestabs DHA is also beneficial in improving the nutritional status of women prior to conception.

CONTRAINDICATIONS

C ontraindications: This product is contraindicated in patients with a known hypersensitivity to any of the ingredients .

WARNINGS

W arnings: Ingestion of more than 3 grams of omega-fatty acids per day has been shown to have potential antithrombotic effects, including increased bleeding time and INR. Administration of omega-3 fatty acids should be avoided in patients on anticoagulants and in those known to have an inherited or acquired bleeding diathesis.

Folic acid alone is improper therapy in the treatment of pernicious anemia and other megaloblastic anemias where vitamin B12 is deficient.

BOXED WARNING

WARNING: Accidental overdose of iron-containing products is a leading cause of fatal poisoning in children under 6. KEEP THIS PRODUCT OUT OF THE REACH OF CHILDREN. In case of accidental overdose, call a doctor or poison control center immediately.

PRECAUTIONS

P recautions: Folic acid in doses above 0.1mg daily may obscure pernicious anemia in that hematologic remission can occur while neurological manifestations remain progressive. This product contains formate, which if consumed above the recommended level, could cause visual impairment and other health effects. Do not take more than the recommended amount. If you are pregnant, nursing, or taking any medications consult your doctor before use. Discontinue use and consult your doctor if any adverse reactions occur. Not intended for use by persons under the age of 18.

ADVERSE REACTIONS

A dverse Reactions: Allergic sensitization has been reported following both oral and parenteral administration of folic acid.

DOSAGE AND ADMINISTRATION

D osage and Administration: Nestabs DHA - One tablet and one soft gel capsule daily or as directed by a physician.

HOW SUPPLIED

H ow Supplied: Nestabs DHA tablets for oral administration are supplied as six child-resistant blister cards containing 5 tablets and 5 softgel capsules each (NDC# 50967-317-30).